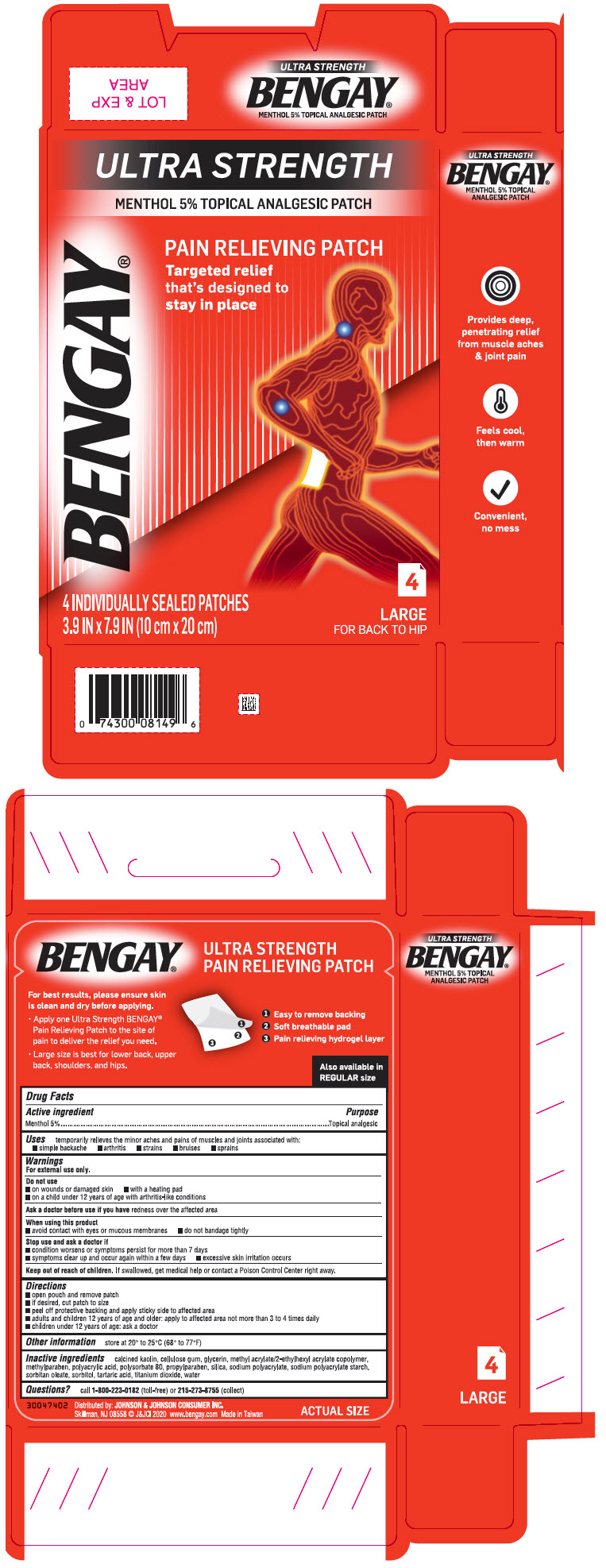 DRUG LABEL: Bengay Ultra Strength
NDC: 69968-0487 | Form: PATCH
Manufacturer: Kenvue Brands LLC
Category: otc | Type: HUMAN OTC DRUG LABEL
Date: 20241106

ACTIVE INGREDIENTS: MENTHOL, UNSPECIFIED FORM 50 mg/1 1
INACTIVE INGREDIENTS: KAOLIN; CARBOXYMETHYLCELLULOSE SODIUM, UNSPECIFIED FORM; GLYCERIN; METHYLPARABEN; POLYACRYLIC ACID (8000 MW); POLYSORBATE 80; PROPYLPARABEN; SILICON DIOXIDE; SODIUM POLYACRYLATE (8000 MW); SORBITAN MONOOLEATE; SORBITOL; TARTARIC ACID; TITANIUM DIOXIDE; WATER

BENGAY® ULTRA STRENGTH PAIN RELIEVING PATCH
Large Size

Drug Facts

Active ingredient

Menthol 5%

Purpose

Topical analgesic

Uses

temporarily relieves minor aches and pains of muscles and joints associated with:

- simple backache
- arthritis
- strains
- bruises
- sprains

Warnings

For external use only.

Do not use

- on wounds or damaged skin
- with a heating pad
- on a child under 12 years of age with arthritis-like conditions

Ask a doctor before use if you have redness over the affected area

When using this product

- avoid contact with eyes or mucous membranes
- do not bandage tightly

Stop use and ask a doctor if

- condition worsens or symptoms persist for more than 7 days
- symptoms clear up and occur again within a few days
- excessive skin irritation occurs

Keep out of reach of children. If swallowed, get medical help or contact a Poison Control Center right away.

Directions

- open pouch and remove patch
- if desired, cut patch to size
- peel off protective backing and apply sticky side to affected area
- adults and children 12 years of age and older: apply to affected area not more than 3 to 4 times daily
- children under 12 years of age: ask a doctor

Other information

- store at 20° to 25°C (68° to 77°F)

Inactive ingredients

calcined kaolin, cellulose gum, glycerin, methyl acrylate/2-ethylhexyl acrylate copolymer, methylparaben, polyacrylic acid, polysorbate 80, propylparaben, silica, sodium polyacrylate, sodium polyacrylate starch, sorbitan oleate, sorbitol, tartaric acid, titanium dioxide, water

Questions?

call 1-800-223-0182 (toll-free) or 215-273-8755 (collect)

Distributed by: JOHNSON & JOHNSON CONSUMER INC.
Skillman, NJ 08558

PRINCIPAL DISPLAY PANEL - 4 Patch Pouch Carton

ULTRA STRENGTH
MENTHOL 5% TOPICAL ANALGESIC PATCH
BENGAY®

PAIN RELIEVING PATCH
Targeted relief
that's designed to
stay in place

4 INDIVIDUALLY SEALED PATCH
3.9 IN x 7.9 IN (10 cm x 20 cm)

4
LARGE
FOR BACK TO HIP